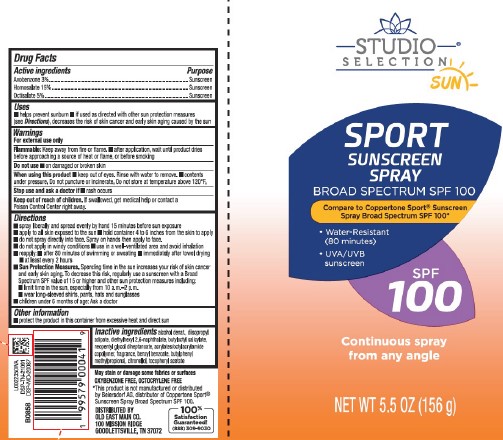 DRUG LABEL: Sport Sunscreen SPF 100
NDC: 75712-979 | Form: AEROSOL, SPRAY
Manufacturer: OLD EAST MAIN CO.
Category: otc | Type: HUMAN OTC DRUG LABEL
Date: 20251027

ACTIVE INGREDIENTS: AVOBENZONE 30 mg/1 g; HOMOSALATE 150 mg/1 g; OCTISALATE 50 mg/1 g
INACTIVE INGREDIENTS: ACRYLATE/ISOBUTYL METHACRYLATE/N-TERT-OCTYLACRYLAMIDE COPOLYMER (40000 MW); BENZYL BENZOATE; DIETHYLHEXYL 2,6-NAPHTHALATE; BUTYLOCTYL SALICYLATE; .BETA.-CITRONELLOL, (R)-; .ALPHA.-TOCOPHEROL ACETATE; BUTYLPHENYL METHYLPROPIONAL; NEOPENTYL GLYCOL DIHEPTANOATE; ALCOHOL; DIISOPROPYL ADIPATE

Studio Selection D79.000/D79AA
Sport Sunscreen Spray SPF 100

Active ingredients

Avobenzone 3%

Homosalate 15%

Octisalate 5%

Purpose

Sunscreen

Uses

- helps prevent sunburn
- if used as directed with other sun protection measures (see Directions), decreases the risk of skin cancer and early skin aging caused by the sun

Warnings

For external use only

Flammable: Keep away from fire or flame.

- after application, wait until product dries before approaching a source of heat or flame, or before smoking

Do not use

- on damaged or broken skin

When using this product

- keep out of eyes. Rinse with water to remove.
- contents under pressure. Do not puncture or incinerate. Do not store at temperature above 120ºF.

Stop use and ask a doctor if

- rash occurs

Keep out of reach of children.

If swallowed, get medical help or contact a Poison Control Center right away.

Directions

- spray liberally and spread evenly by hand 15 minutes before sun exposure
- apply to all skin exposed to the sun
- hold container 4 to 6 inches from the skin to apply
- do not spray directly into face. Spray on hands then apply to face.
- do not apply in windy conditions
- use in a well-ventilated area and avoid inhalation
- reapply:
- after 80 minutes of swimming or sweating
- immediately after towel drying
- at least every 2 hours
- Sun Protection Measures. Spending time in the sun increases your risk of skin cancer and early skin aging. To decrease this risk, regularly use a sunscreen with a Broad Spectrum SPF value of 15 or higher and other sun protection measures including:
- limit time in the sun, especially from 10 a.m.–2 p.m.
- wear long-sleeved shirts, pants, hats and sunglasses
- children under 6 months of age: Ask a doctor

Other information

- protect the product in this container from excessive heat and direct sun

Inactive ingredients

alcohol denat., diisopropyl adipate, diethylhexyl 2,6-naphthalate, butyloctyl salicylate, neopentyl glycol diheptanoate, acrylates/octylacrylamide copolymer, fragrance, benzyl benzoate, butylphenyl methylpropional, citronellol, tocopheryl acetate

Disclaimers

May stain or damage some fabrics or surfaces

OXYBENZONE FREE, OCTOCRYLENE FREE

*This product is not manufactured or distributed by Beiersdorf AG, distributor of Coppertone Sport® Sunscreen Spray Broad Spectrum SPF 100.

Adverse Reactions

DISTRIBUTED BY OLD EAST MAIN CO.

100 MISSION RIDGE

GOODLETTSVILLE, TN 37072

100% Satisfaction Guaranteed!

(888) 309-9030

DSP-TN-21091

DSP-MO-20087

Principal Display Panel

STUDIO SELECTION®

SUN

SPORT

SUNSCREEN SPRAY

BROAD SPECTRUM SPF 100

Compare to Coppertone Sport® Sunscreen Spray Broad Spectrum SPF 100*

- Water-Resistant (80 minutes)
- UVA/UVB sunscreen

SPF 100

Continuous spray from any angle

NET WT. 5.5 OZ (156 g)